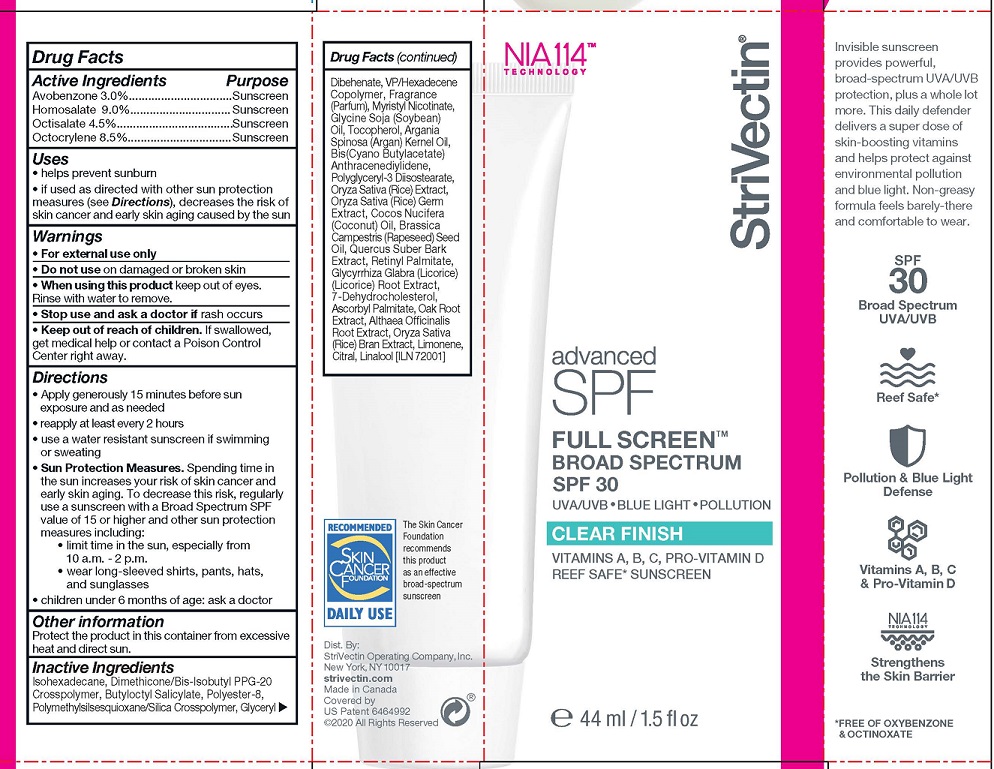 DRUG LABEL: StriVectin Advanced SPF Full Screen
NDC: 54291-051 | Form: LOTION
Manufacturer: Canadian Custom Packaging Company
Category: otc | Type: HUMAN OTC DRUG LABEL
Date: 20241211

ACTIVE INGREDIENTS: AVOBENZONE 3 g/100 mL; HOMOSALATE 9 g/100 mL; OCTISALATE 4.5 g/100 mL; OCTOCRYLENE 8.5 g/100 mL
INACTIVE INGREDIENTS: ISOHEXADECANE; DIMETHICONE/BIS-ISOBUTYL PPG-20 CROSSPOLYMER; BUTYLOCTYL SALICYLATE; POLYESTER-8 (1400 MW, CYANODIPHENYLPROPENOYL CAPPED); POLYMETHYLSILSESQUIOXANE (4.5 MICRONS); SILICA, TRIMETHYLSILYL CAPPED; GLYCERYL DIBEHENATE; VINYLPYRROLIDONE/HEXADECENE COPOLYMER; MYRISTYL NICOTINATE; SOYBEAN OIL; TOCOPHEROL; ARGAN OIL; BUTYL ACETATE; POLYGLYCERYL-3 DIISOSTEARATE; ORYZA SATIVA WHOLE; COCONUT OIL; CANOLA OIL; QUERCUS SUBER BARK; VITAMIN A PALMITATE; LICORICE; 7-DEHYDROCHOLESTEROL; ASCORBYL PALMITATE; QUERCUS SPP. WHOLE; ALTHAEA OFFICINALIS ROOT; LIMONENE, (+)-; CITRAL; LINALOOL, (+)-

StriVectin Advanced SPF Full Screen - Clear Finish

ACTIVE INGREDIENTS

Avobenzone 3.0%
Homosalate 9.0%
Octisalate 4.5%
Octocrylene 8.5%

PURPOSE

Sunscreen

USES

- helps prevent sunburn
- if used as directed with other sun protection measures (see Directions), decreases the risk of skin cancer and early skin aging caused by the sun

WARNINGS

- For external use only
- Do not use on damaged or broken skin
- When using this product keep out of eyes. Rinse with water to remove.
- Stop use and ask a doctor if rash occurs

Keep out of reach of children.

If swallowed, get medical help or contact
a Poison Control Center right away.

- Keep out of reach of children. If swallowed, get medical help or contact a Poison Control Center right away.

DIRECTIONS

- Apply generously 15 minutes before sun exposure and as needed
- reapply at least every 2 hours
- use a water resistant sunscreen if swimming or sweating
- Sun Protection Measures. Spending time inthe sun increases your risk of skin cancer andearly skin aging. To decrease this risk, regularly use a sunscreen with a Broad Spectrum SPFvalue of 15 or higher and other sun protectionmeasures including:
- limit time in the sun, especially from 10 a.m. - 2 p.m.
- wear long-sleeved shirts, pants, hats,and sunglasses
- children under 6 months of age: ask a doctor

OTHER INFORMATION

Protect the product in this container from excessive heat and direct sun.

INACTIVE INGREDIENTS

Isohexadecane, Dimethicone/Bis-Isobutyl PPG-20 Crosspolymer, Butyloctyl Salicylate, Polyester-8, Polymethylsilsesquioxane/Silica Crosspolymer, Glyceryl Dibehenate, VP/Hexadecene Copolymer, Fragrance (Parfum), Myristyl Nicotinate, Glycine Soja (Soybean) Oil, Tocopherol, Argania Spinosa (Argan) Kernel Oil, Bis(Cyano Butylacetate) Anthracenediylidene, Polyglyceryl-3 Diisostearate, Oryza Sativa (Rice) Extract, Oryza Sativa (Rice) Germ Extract, Cocos Nucifera (Coconut) Oil, Brassica Campestris (Rapeseed) Seed Oil, Quercus Suber Bark Extract, Retinyl Palmitate, Glycyrrhiza Glabra (Licorice) (Licorice) Root Extract, 7-Dehydrocholesterol, Ascorbyl Palmitate, Oak Root Extract, Althaea Officinalis Root Extract, Oryza Sativa (Rice) Bran Extract, Limonene, Citral, Linalool